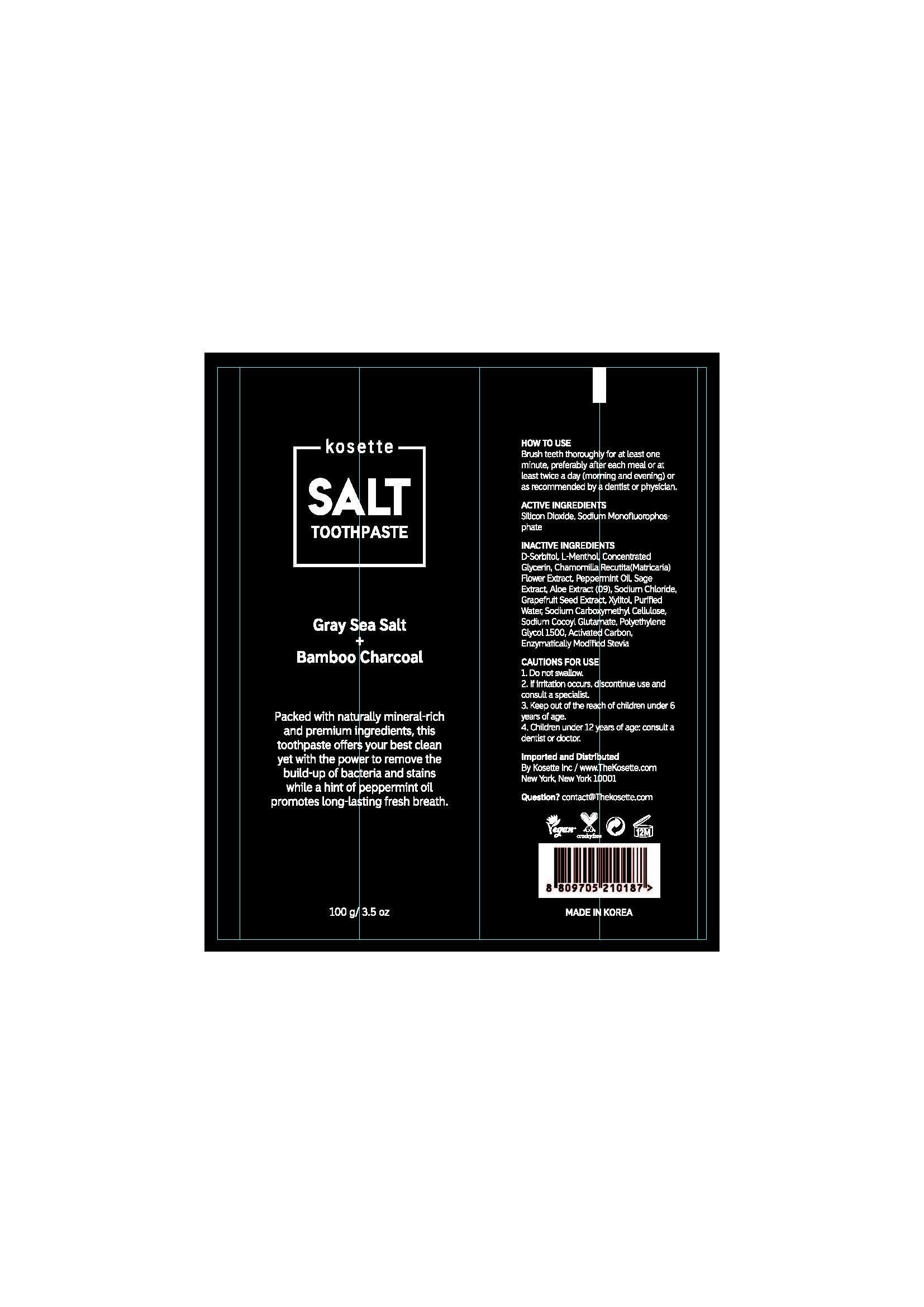 DRUG LABEL: Kosette Salt Tooth
NDC: 74724-0010 | Form: PASTE, DENTIFRICE
Manufacturer: K.Boeun Pharmaceutical Co.,Ltd.
Category: otc | Type: HUMAN OTC DRUG LABEL
Date: 20200527

ACTIVE INGREDIENTS: SODIUM MONOFLUOROPHOSPHATE 0.76 g/100 g
INACTIVE INGREDIENTS: WATER; SILICON DIOXIDE; SORBITOL; XYLITOL

ACTIVE INGREDIENT

SODIUM MONOFLUOROPHOSPHATE

PURPOSE

ANTI-CAVITY

Keep out of reach of children

INDICATIONS AND USAGE

Brush teeth thoroughly for at least one minute, preferably after each meal or at least twice a day (morning and evening) or as recommended by a dentist or physician

WARNINGS

Storage method

1. Keep it at room temperature in a classified container.

2. Cover and store at room temperature.

3. Store in a not moisture and cool place.

4. Air may come out during use of this product, but there is no problem with its weight.

Usage Precautions

1. Be careful not to swallow. Rinse mouth thoroughly after use

2. If the use of toothpaste causes abnormalities such as gums or mouth injury, discontinue use and consult a doctor or dentist.

3. For children under 6 years of age, use a small amount of toothpaste as small as pea per use, and use under the guidance of a guardian to avoid sucking or swallowing.

4. If a child under 6 years old swallows large amount, consult with a doctor or dentist immediately.

5. Keep out of the reach of children under 6 years of age.

INACTIVE INGREDIENT

D-Sorbitol Solution, WATER, SILICON DIOXIDE, CONCENTRATED GLYCERIN, SODIUM COCOYL GLUTAMATE, POLYETHYLENE GLYCOL 1500, CARBOXYMETHYLCELLULOSE SODIUM, PEPPERMINT OIL, ACTIVE CARBON, L-MENTHOL, CITRUS PARADISI (GRAPEFRUIT) SEED EXTRACT, XYLITOL, SODIUM CHLORIDE, ENZYMATICALLY MODIFIED STEVIA, CHAMOMILLA RECUTITA (MATRICARIA) FLOWER EXTRACT, ALOE EXTRACT, SAGE EXTRACT

DOSAGE AND ADMINISTRATION

For dental use only